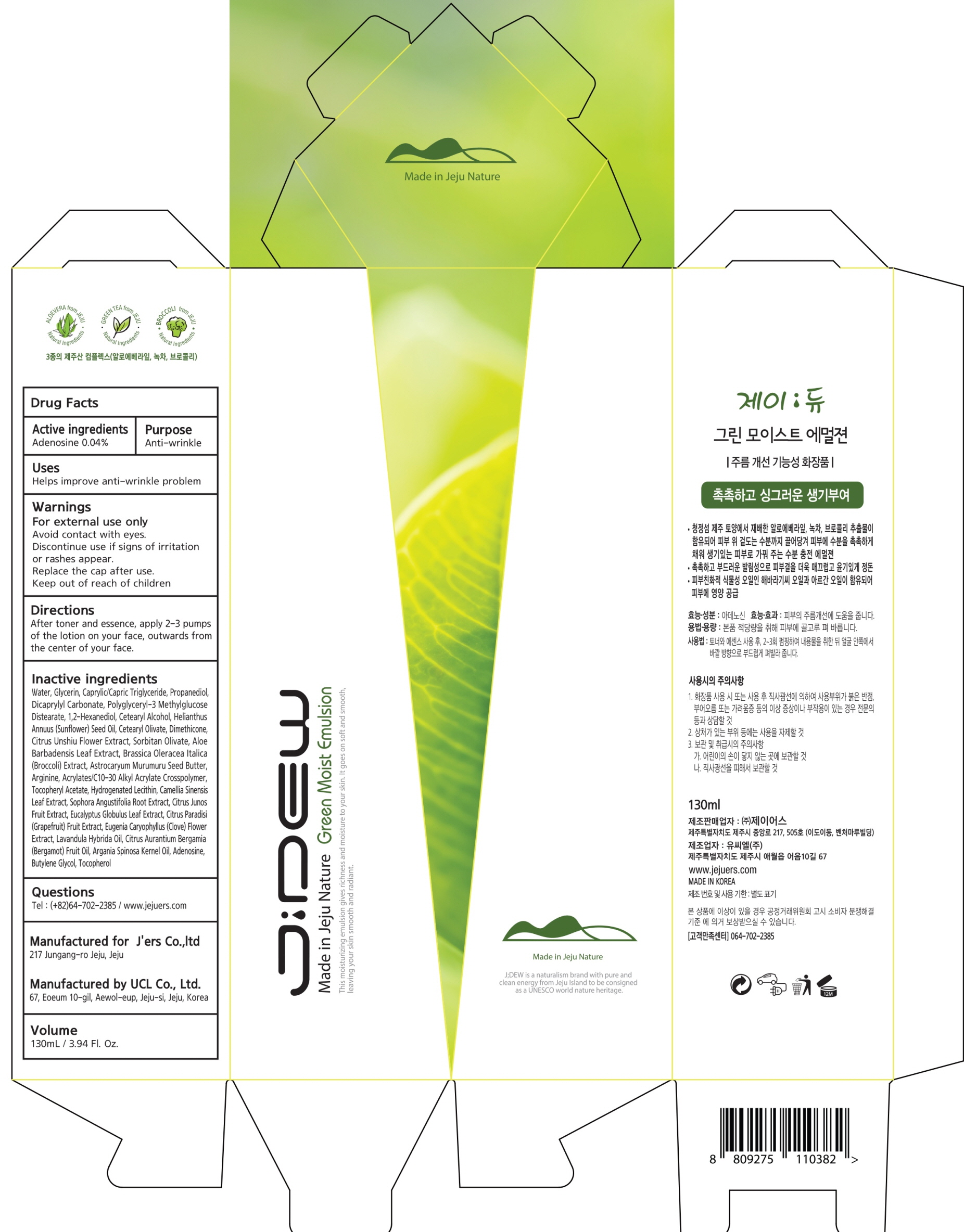 DRUG LABEL: JDEW GREEN MOIST
NDC: 72543-030 | Form: EMULSION
Manufacturer: J'ers Co.,ltd
Category: otc | Type: HUMAN OTC DRUG LABEL
Date: 20180918

ACTIVE INGREDIENTS: Adenosine 0.05 g/130 mL
INACTIVE INGREDIENTS: WATER; GLYCERIN

ACTIVE INGREDIENT

Active ingredients: Adenosine 0.04%

INACTIVE INGREDIENT

Inactive ingredients:

Water, Glycerin, Caprylic/Capric Triglyceride, Propanediol, Dicaprylyl Carbonate, Polyglyceryl-3 Methylglucose Distearate, 1,2-Hexanediol, Cetearyl Alcohol, Helianthus Annuus (Sunflower) Seed Oil, Cetearyl Olivate, Dimethicone, Citrus Unshiu Flower Extract, Sorbitan Olivate, Aloe Barbadensis Leaf Extract, Brassica Oleracea Italica (Broccoli) Extract, Astrocaryum Murumuru Seed Butter, Arginine, Acrylates/C10-30 Alkyl Acrylate Crosspolymer, Tocopheryl Acetate, Hydrogenated Lecithin, Camellia Sinensis Leaf Extract, Sophora Angustifolia Root Extract, Citrus Junos Fruit Extract, Eucalyptus Globulus Leaf Extract, Citrus Paradisi (Grapefruit) Fruit Extract, Eugenia Caryophyllus (Clove) Flower Extract, Lavandula Hybrida Oil, Citrus Aurantium Bergamia (Bergamot) Fruit Oil, Argania Spinosa Kernel Oil, Adenosine, Butylene Glycol, Tocopherol

PURPOSE

Purpose: Anti-wrinkle

WARNINGS

- For external use only

- Avoid contact with eyes.

- Discontinue use if signs of irritation or rashes appear.

- Replace the cap after use.

- Keep out of reach of children

KEEP OUT OF REACH OF CHILDREN

Uses

Helps improve anti-wrinkle problem

Directions

After toner and essence, apply 2-3 pumps of the lotion on your face, outwards from the center of your face.